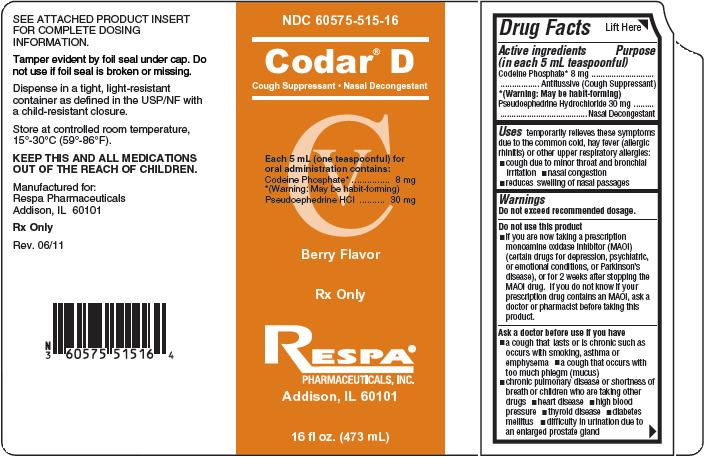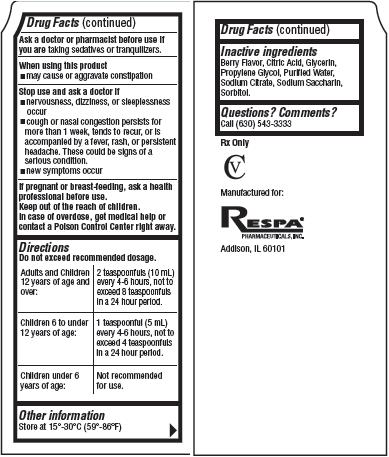 DRUG LABEL: CODAR 
NDC: 60575-515 | Form: LIQUID
Manufacturer: Respa Pharmaceuticals
Category: otc | Type: HUMAN OTC DRUG LABEL
Date: 20110726
DEA Schedule: CV

ACTIVE INGREDIENTS: Codeine Phosphate 8 mg/5 mL; Pseudoephedrine Hydrochloride 30 mg/5 mL
INACTIVE INGREDIENTS: Citric Acid; Glycerin; Propylene Glycol; Water; Sodium Citrate; Saccharin Sodium; Sorbitol

Codar D

Drug Facts

Active ingredients
(in each 5 mL teaspoonful)
Codeine Phosphate* 8 mg
*(Warning: May be habit-forming)
Pseudoephedrine Hydrochloride 30 mg

Purpose

Cough Suppressant
Nasal Decongestant

Uses

temporarily relieves these symptoms due to the common cold, hay fever (allergic rhinitis) or other upper respiratory allergies:

- cough due to minor throat and bronchial irritation
- nasal congestion
- reduces swelling of nasal passages

Warnings

Do not exceed recommended dosage.

Do not use this product

- if you are now taking a prescription monoamine oxidase inhibitor (MAOI) (certain drugs for depression, psychiatric, or emotional conditions, or Parkinson's disease), or for 2 weeks after stopping the MAOI drug. If you do not know if your prescription drug contains an MAOI, ask a doctor or pharmacist before taking this product.

Ask a doctor before use if you have

- a cough that lasts or is chronic such as occurs with smoking, asthma or emphysema
- a cough that occurs with too much phlegm (mucus)
- chronic pulmonary disease or shortness of breath or children who are taking other drugs
- heart disease
- high blood pressure
- thyroid disease
- diabetes mellitus
- difficulty in urination due to an enlarged prostate gland

Ask a doctor or pharmacist before use if you are

taking sedatives or tranquilizers.

When using this product

- may cause or aggravate constipation

Stop use and ask a doctor if

- nervousness, dizziness, or sleeplessness occur
- cough or nasal congestion persists for more than 1 week, tends to recur, or is accompanied by a fever, rash, or persistent headache. These could be signs of a serious condition.
- new symptoms occur

If pregnant or breast-feeding,

ask a health professional before use.

Keep out of reach of children.

In case of overdose, get medical help or contact a Poison control Center right away.

Directions

Do not exceed recommended dosage.

Adults and Children 12 years of age and over: | 2 teaspoonfuls (10 mL) every 4-6 hours, not to exceed 8 teaspoonfuls in a 24 hour period.
Children 6 to under 12 years of age: | 1 teaspoonful (5 mL) every 4-6 hours, not to exceed 4 teaspoonfuls in a 24 hour period.
Children under 6 years of age: | Not recommended for use.

Other information

Store at 15°- 30°C (59°- 86°F)

Inactive ingredients

Berry Flavor, Citric Acid, Glycerin, Propylene Glycol, Purified Water, Sodium Citrate, Sodium Saccharin, Sorbitol

Questions? Comments?

Call (630) 543-3333
Rx Only
CV
Manufactured for:
RESPA®
PHARMACEUTICALS, INC.
Addison, IL 60101

Product Packaging

The packaging below represents the labeling currently used:
Principal display panel and side pane for 473 mL label:
NDC 60575-515-16
_____________________________________
Codar® D
Cough Suppressant / Nasal Decongestant
_____________________________________
CV
Each 5 mL (one teaspoonful) for oral
administration contains:
Codeine Phosphate*..............................8 mg
Pseudoephedrine HCl...........................30 mg
Berry Flavor
Rx Only
RESPA®
PHARMACEUTICALS, INC.
Addison, IL 60101
16 fl oz. (473 mL)
SEE ATTACHED PRODUCT INSERT FOR
COMPLETE DOSING INFORMATION.
Tamper evident by foil seal under cap. Do
not use if foil seal is broken or missing.
Dispense in a tight, light-resistant container
as defined in the USP/NF with a child-resistant
closure.
Store at controlled room temperature, 15°- 30°C
(59°- 86°F).
KEEP THIS AND ALL MEDICATIONS OUT
OF THE REACH OF CHILDREN.
Manufactured for:
Respa Pharmaceuticals
Addison, IL 60101
Rx Only
Rev. 06/11